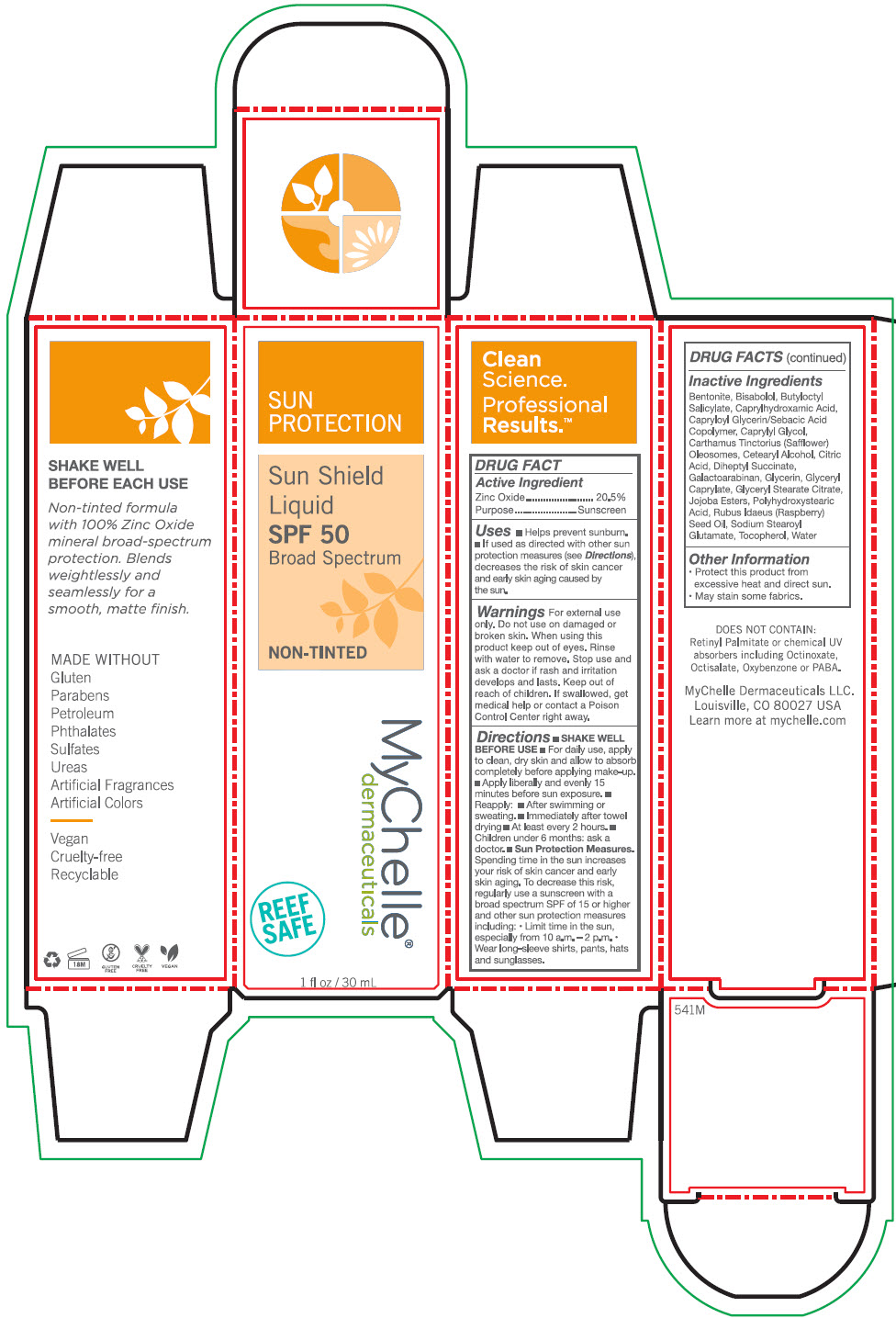 DRUG LABEL: MyChelle Dermaceuticals Sun Shield Non-Tinted 
NDC: 72805-080 | Form: LIQUID
Manufacturer: French Transit, Ltd.
Category: otc | Type: HUMAN OTC DRUG LABEL
Date: 20190909

ACTIVE INGREDIENTS: Zinc Oxide 20.5 g/100 mL
INACTIVE INGREDIENTS: Water; Bentonite; Levomenol; Butyloctyl Salicylate; Caprylhydroxamic Acid; Capryloyl Glycerin/Sebacic Acid Copolymer (2000 MPA.S); Caprylyl Glycol; Carthamus Tinctorius Seed Oleosomes; Cetostearyl Alcohol; Anhydrous Citric Acid; Diheptyl Succinate; Galactoarabinan; Glycerin; Glyceryl Monocaprylate; Glyceryl Stearate Citrate; Hydrogenated Jojoba Oil, Randomized; Polyhydroxystearic Acid (2300 MW); Raspberry Seed Oil; Sodium Stearoyl Glutamate; Tocopherol

MyChelle® Dermaceuticals Sun Shield Liquid Non-Tinted SPF 50 Broad Spectrum

DRUG FACTS

Active Ingredient

Zinc Oxide 20.5%

Purpose

Sunscreen

Uses

- Helps prevent sunburn.
- If used as directed with other sun protection measures (see Directions), decreases the risk of skin cancer and early skin aging caused by the sun.

Warnings

For external use only. Do not use on damaged or broken skin. When using this product keep out of eyes. Rinse with water to remove. Stop use and ask a doctor if rash and irritation develops and lasts.

Keep out of reach of children. If swallowed, get medical help or contact a Poison Control Center right away.

Directions

- SHAKE WELL BEFORE USE.
- For daily use, apply to clean, dry skin and allow to absorb completely before applying make-up.
- Apply liberally 15 minutes before sun exposure.
- Reapply After 80 minutes of swimming or sweating.
- Immediately after towel drying. At least every 2 hours.
- Children under 6 months: ask a doctor.
- Sun Protection Measures. Spending time in the sun increases your risk of skin cancer and early skin aging. To decrease this risk, regularly use a sunscreen with a broad spectrum SPF of 15 or higher and other sun protection measures including:
  - Limit time in the sun, especially from 10 a.m. – 2 p.m.
  - Wear long-sleeve shirts, pants, hats and sunglasses.

Inactive Ingredients

Bentonite, Bisabolol, Butyloctyl Salicylate, Caprylhydroxamic Acid, Capryloyl Glycerin/Sebacic Acid Copolymer, Caprylyl Glycol, Carthamus Tinctorius (Safflower) Oleosomes, Cetearyl Alcohol, Citric Acid, Diheptyl Succinate, Galactoarabinan, Glycerin, Glyceryl Caprylate, Glyceryl Stearate Citrate, Jojoba Esters, Polyhydroxystearic Acid, Rubus Idaeus (Raspberry) Seed Oil, Sodium Stearoyl Glutamate, Tocopherol, Water

Other Information

- Protect this product from excessive heat and direct sun.
- May stain some fabrics

PRINCIPAL DISPLAY PANEL - 30 mL Bottle Box

SUN
PROTECTION

Sun Shield
Liquid
SPF 50
Broad Spectrum

NON-TINTED

MyChelle®
dermaceuticals

REEF
SAFE

1 fl oz / 30 mL